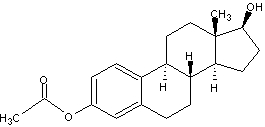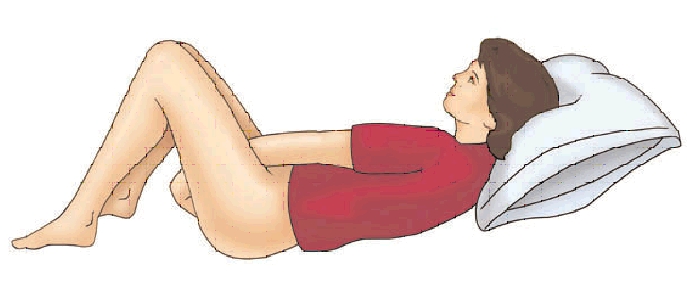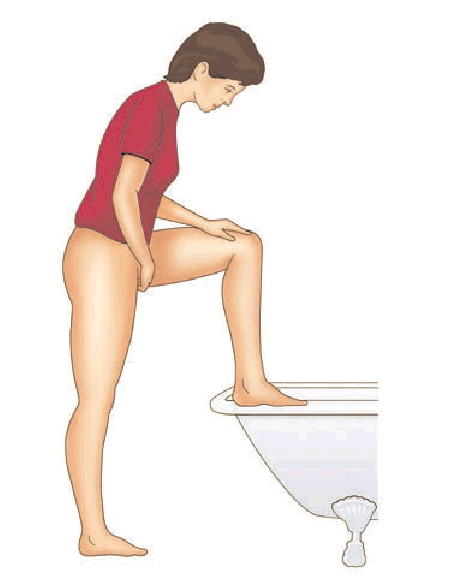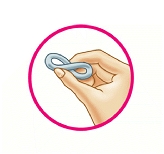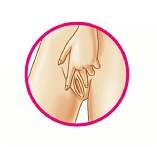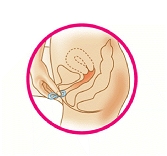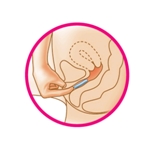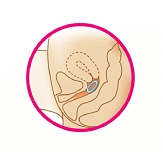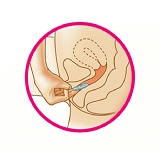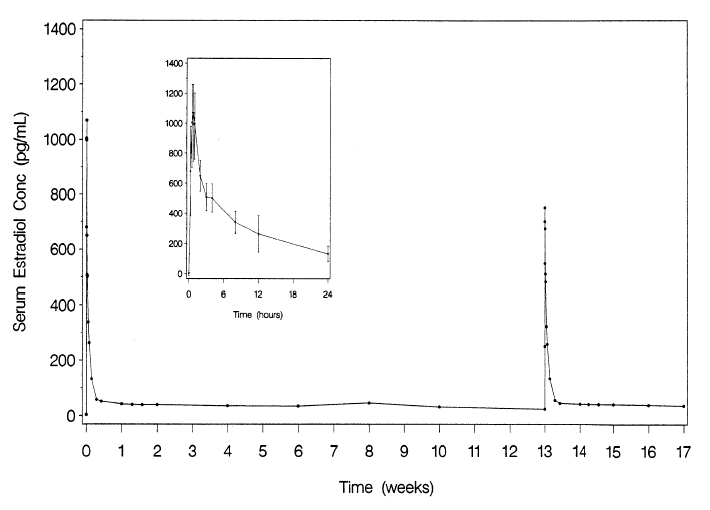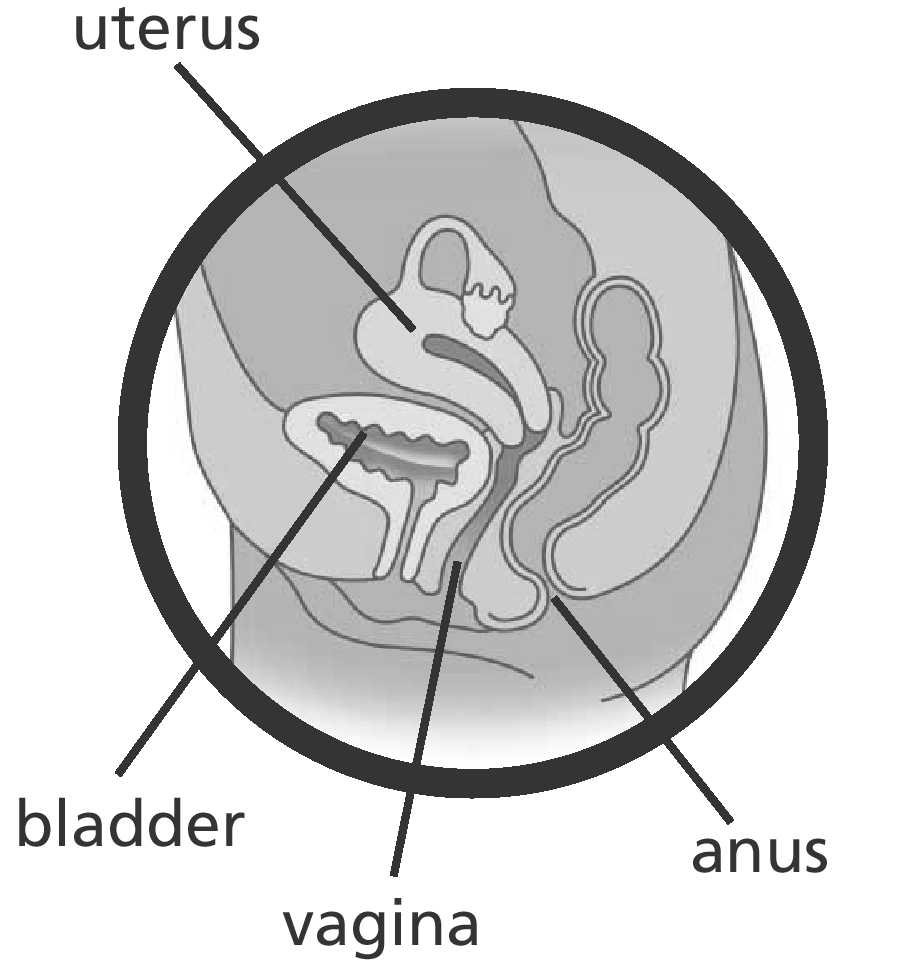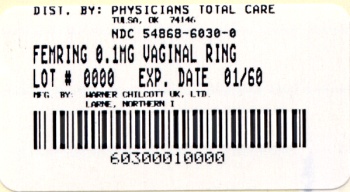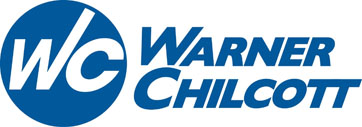 DRUG LABEL: Femring
NDC: 54868-6030 | Form: RING
Manufacturer: Physicians Total Care, Inc.
Category: prescription | Type: HUMAN PRESCRIPTION DRUG LABEL
Date: 20100603

ACTIVE INGREDIENTS: ESTRADIOL ACETATE 0.1 mg/24 [USP'U]
INACTIVE INGREDIENTS: BARIUM SULFATE; DIMETHICONE; SILICON DIOXIDE

BOXED WARNING

WARNING: ENDOMETRIAL CANCER, CARDIOVASCULAR DISORDERS AND PROBABLE DEMENTIA FOR ESTROGEN-ALONE THERAPY

ENDOMETRIAL CANCER

There is an increased risk of endometrial cancer in a woman with a uterus who uses unopposed estrogens. Adding a progestin to estrogen therapy has been shown to reduce the risk of endometrial hyperplasia, which may be a precursor to endometrial cancer. Adequate diagnostic measures, including directed or random endometrial sampling when indicated, should be undertaken to rule out malignancy in postmenopausal women with undiagnosed persistent or recurring abnormal genital bleeding. (See WARNINGS, Malignant neoplasms, Endometrial cancer.)

CARDIOVASCULAR DISORDERS AND PROBABLE DEMENTIA

Estrogen-alone therapy should not be used for the prevention of cardiovascular disease or dementia. (See CLINICAL STUDIES and WARNINGS, Cardiovascular disorders and Dementia.)

The Women's Health Initiative (WHI) estrogen-alone substudy reported increased risks of stroke and deep vein thrombosis (DVT) in postmenopausal women (50 to 79 years of age) during 7.1 years of treatment with daily oral conjugated estrogens (CE) [0.625 mg], relative to placebo. (See CLINICAL STUDIES and WARNINGS, Cardiovascular disorders.)

The Women’s Health Initiative Memory Study (WHIMS) estrogen-alone ancillary study of the WHI reported increased risk of developing probable dementia in postmenopausal women 65 years of age or older during 5.2 years of treatment with daily CE (0.625 mg)-alone, relative to placebo. It is unknown whether this finding applies to younger postmenopausal women. (See CLINICAL STUDIES and WARNINGS, Dementia and PRECAUTIONS, Geriatric Use.)

In the absence of comparable data, these risks should be assumed to be similar for other doses of CE and other dosage forms of estrogens.

Estrogens with or without progestins should be prescribed at the lowest effective doses and for the shortest duration consistent with treatment goals and risks for the individual woman.

WARNING: CARDIOVASCULAR DISORDERS, BREAST CANCER AND PROBABLE DEMENTIA FOR ESTROGEN PLUS PROGESTIN THERAPY

Estrogens plus progestin therapy should not be used for the prevention of cardiovascular disease or dementia. (See CLINICAL STUDIES and WARNINGS, Cardiovascular disorders, and Dementia.)

The WHI estrogen plus progestin substudy reported increased risks of DVT, pulmonary embolism, stroke, and myocardial infarction in postmenopausal women (50 to 79 years of age) during 5.6 years of treatment with daily oral CE (0.625 mg) combined with medroxyprogesterone acetate (MPA) [2.5 mg], relative to placebo. (See CLINICAL STUDIES and WARNINGS, Cardiovascular disorders.)

The WHI estrogen plus progestin substudy also demonstrated an increased risk of invasive breast cancer. (See CLINICAL STUDIES and WARNINGS, Malignant neoplasms, Breast Cancer.)

The WHIMS estrogen plus progestin ancillary study of the WHI reported an increased risk of developing probable dementia in postmenopausal women 65 years of age or older during 4 years of treatment with daily CE (0.625 mg) combined with MPA (2.5 mg), relative to placebo. It is unknown whether this finding applies to younger postmenopausal women. (See CLINICAL STUDIES and WARNINGS, Dementia and PRECAUTIONS, Geriatric Use.)

In the absence of comparable data, these risks should be assumed to be similar for other doses of CE and MPA therapy and other combinations and dosage forms of estrogens and progestins.

Estrogens with or without progestins should be prescribed at the lowest effective doses and for the shortest duration consistent with treatment goals and risks for the individual woman.

DESCRIPTION

Femring® (estradiol acetate vaginal ring) is an off-white, soft, flexible ring with a central core containing estradiol acetate.

Femring is made of cured silicone elastomer composed of dimethyl polysiloxane silanol, silica (diatomaceous earth), normal propyl orthosilicate, stannous octoate; barium sulfate and estradiol acetate. The rings have the following dimensions: outer diameter 56 mm, cross-sectional diameter 7.6 mm, core diameter 2 mm.

Femring is available in two strengths: Femring 0.05 mg/day has a central core that contains 12.4 mg of estradiol acetate, which releases at a rate equivalent to 0.05 mg of estradiol per day for 3 months. Femring 0.10 mg/day has a central core that contains 24.8 mg of estradiol acetate, which releases at a rate equivalent to 0.10 mg of estradiol per day for 3 months.

Estradiol acetate is chemically described as estra-1,3,5(10)-triene-3,17β-diol-3-acetate. The molecular formula of estradiol acetate is C20H26O3 and the structural formula is:

The molecular weight of estradiol acetate is 314.42.

CLINICAL PHARMACOLOGY

Endogenous estrogens are largely responsible for the development and maintenance of the female reproductive system and secondary sexual characteristics. Although circulating estrogens exist in a dynamic equilibrium of metabolic interconversions, estradiol is the principal intracellular human estrogen and is substantially more potent than its metabolites, estrone and estriol, at the receptor level.

The primary source of estrogen in normally cycling adult women is the ovarian follicle which secretes 70 to 500 mcg of estradiol daily depending on the phase of the menstrual cycle. After menopause, most endogenous estrogen is produced by conversion of androstenedione, secreted by the adrenal cortex, to estrone by peripheral tissues. Thus, estrone and the sulfate conjugated form, estrone sulfate, are the most abundant circulating estrogens in postmenopausal women.

Estrogens act through binding to nuclear receptors in estrogen-responsive tissues. To date, two estrogen receptors have been identified. These vary in proportion from tissue to tissue.

Circulating estrogens modulate the pituitary secretion of the gonadotropins, luteinizing hormone (LH) and follicle stimulating hormone (FSH) through a negative feedback mechanism. Estrogens act to reduce the elevated levels of these hormones seen in postmenopausal women.

Pharmacokinetics A. Absorption

Drug delivery from Femring is rapid for the first hour and then declines to a relatively constant rate for the remainder of the 3-month dosing interval. In vitro studies have shown that this initial release is higher as the rings age upon storage. Estradiol acetate is rapidly hydrolyzed to estradiol which is absorbed through the vaginal mucosa as evidenced by the mean time to maximum concentration (tmax) for estradiol of about 1 hour (range 0.25 to 1.5 hrs). Following the maximum concentration (Cmax), serum estradiol decreases rapidly such that by 24 to 48 hours postdose, serum estradiol concentrations are relatively constant through the end of the 3-month dosing interval, see Figure 1 for results from rings stored for 16 months.

Figure 1. Mean serum estradiol concentrations following multiple dose administration of Femring (0.05 mg/day estradiol) (second dose administered at 13 weeks) (inset: mean (±SD) of serum concentration-time profile for dose 1 from 0-24 hours)

Following administration of Femring (0.05 mg/day estradiol), average serum estradiol concentration was 40.6 pg/mL; the corresponding apparent in vivo estradiol delivery rate was 0.052 mg/day. Following administration of Femring (0.10 mg/day estradiol), average serum estradiol concentration was 76 pg/mL; apparent in vivo delivery rate was 0.097 mg/day. Results are summarized in Table 1 below.

Table 1. Summary of Mean (%RSD)* Pharmacokinetic Parameters for Femring
Dose (as estradiol) |  | Number of subjects | Cmax (pg/mL) | Tmax (hour) | Cavg (pg/mL)
0.05 mg/day | Estradiol† | 25 | 1129 (25) | 0.9 (41) | 40.6 (26)
 | Estrone† | 25 | 141 (25) | 6.2 (84) | 35.9 (21)
 | Estrone sulfate† | 25 | 2365 (44) | 9.3 (39) | 494.6 (48)
0.10 mg/day | Estradiol‡ | 12 | 1665 (23) | 0.7 (90) | --§
 | Estradiol¶ | 11 | -- | -- | 76.0 (24)
 | Estrone¶ | 11 | -- | -- | 45.7 (25)

* Relative Standard Deviation
† Study 1
‡ Study 2
§ Not determined
¶ Study 3

Consistent with the avoidance of first pass metabolism achieved by vaginal estradiol administration, serum estradiol concentrations were slightly higher than estrone concentrations.

B. Distribution

The distribution of exogenous estrogens is similar to that of endogenous estrogens. Estrogens are widely distributed in the body and are generally found in higher concentrations in the sex hormone target organs. Estrogens circulate in the blood largely bound to sex hormone binding globulin (SHBG) and to albumin.

C. Metabolism

Exogenous estrogens are metabolized in the same manner as endogenous estrogens. Circulating estrogens exist in a dynamic equilibrium of metabolic interconversions. These transformations take place mainly in the liver. Estradiol is converted reversibly to estrone, and both can be converted to estriol, which is the major urinary metabolite. Estrogens also undergo enterohepatic recirculation via sulfate and glucuronide conjugation in the liver, biliary secretion of conjugates into the intestine, and hydrolysis in the gut followed by reabsorption. In postmenopausal women, a significant proportion of the circulating estrogens exist as sulfate conjugates, especially estrone sulfate, which serves as a circulating reservoir for the formation of more active estrogens.

D. Excretion

Estradiol, estrone, and estriol are excreted in the urine along with glucuronide and sulfate conjugates.

E. Special Populations

No pharmacokinetic studies were conducted in special populations, including patients with renal or hepatic impairment.

F. Drug Interactions

In vitro and in vivo studies have shown that estrogens are metabolized partially by cytochrome P450 3A4 (CYP3A4). Therefore, inducers or inhibitors of CYP3A4 may affect estrogen drug metabolism. Inducers of CYP3A4 such as St. John’s Wort preparations (Hypericum perforatum), phenobarbital, carbamazepine and rifampin may reduce plasma concentrations of estrogens, possibly resulting in a decrease in therapeutic effects and/or changes in the uterine bleeding profile. Inhibitors of CYP3A4 such as erythromycin, clarithromycin, ketoconazole, itraconazole, ritonavir and grapefruit juice may increase plasma concentrations of estrogens and may result in side effects.

CLINICAL STUDIES

Effects on vasomotor symptoms

A 13-week double-blind, placebo-controlled clinical trial was conducted to evaluate the efficacy of 2 doses of the vaginal ring in the treatment of moderate to severe vasomotor symptoms in 333 postmenopausal women between 29 and 85 years of age (mean age 51.7 years, 77% were Caucasian) who had at least 7 moderate to severe hot flushes daily or at least 56 moderate to severe hot flushes per week before randomization. Patients were randomized to receive either placebo, Femring 0.05 mg/day or Femring 0.10 mg/day. Femring 0.05 mg/day and Femring 0.10 mg/day were shown to be statistically better than placebo at weeks 4 and 12 for relief of both the frequency and severity of moderate to severe vasomotor symptoms. Frequency results are shown in Table 2. Severity results are shown in Table 3.

Table 2. Mean Change from Baseline in the Number of Moderate to Severe Vasomotor Symptoms per Week – ITT Population, LOCF
Visit | Placebo (n = 105) | Estradiol 0.05 mg/day (n = 111) | Estradiol 0.10 mg/day (n = 109)
Baseline*
Mean (SD) | 83.62 (60.42) | 73.83 (24.53) | 75.11 (25.44)
Week 4
Mean (SD) | 51.14 (51.19) | 21.59† (27.76) | 11.37† (19.43)
Mean Change from Baseline (SD) | -32.48 (46.25) | -52.24† (32.92) | -63.75† (26.68)
p value vs. Placebo (95% CI)‡ | - | less than 0.001 (-30.7, -8.8) | less than 0.001 (-42.2, -20.3)
Week 12
Mean (SD) | 42.21 (41.13) | 15.48† (25.42) | 8.25† (16.58)
Mean Change from Baseline (SD) | -41.41 (65.61) | -58.36† (31.36) | -66.87† (27.44)
p value vs. Placebo (95% CI)‡ | - | 0.006 (-30.5, -3.4) | less than 0.001 (-39.1, -11.8)

ITT = intent to treat; LOCF = last observation carried forward; CI = confidence interval
* The baseline number of moderate to severe vasomotor symptoms (MSVS) is the weekly
average number of MSVS during the two weeks between screening and randomization.
† Denotes statistical significance at the 0.050 level.
‡ p values and confidence intervals are from a two-way ANOVA with factors for treatment
and study center for the difference between treatment groups in the mean change from baseline.
Confidence intervals are adjusted for multiple comparisons within each timepoint using Dunnett’s
method

Table 3. Mean Change from Baseline in the Severity of Moderate to Severe Vasomotor Symptoms per Week – ITT Population, LOCF
Visit | Placebo (n = 105) | Estradiol 0.05 mg/day (n = 111) | Estradiol 0.10 mg/day (n = 109)
Baseline*
Mean (SD) | 2.51 (0.26) | 2.46 (0.23) | 2.48 (0.24)
Week 4
Mean (SD) | 2.23 (0.71) | 1.67† (1.07) | 1.15† (1.14)
Mean Change from Baseline (SD) | -0.28 (0.69) | - 0.79† (1.08) | -1.33† (1.10)
p value vs. Placebo (95% CI)‡ | - | less than 0.001 (-0.8, -0.2) | less than 0.001 (-1.3, -0.8)
Week 12
Mean (SD) | 2.00 (0.96) | 1.41† (1.17) | 0.92† (1.09)
Mean Change from Baseline (SD) | -0.51 (0.94) | -1.06† (1.16) | -1.56† (1.06)
p value vs. Placebo (95% CI)‡ | - | less than 0.001 (-0.9, -0.2) | less than 0.001 (-1.4, -0.7)

ITT = intent to treat; LOCF = last observation carried forward; CI = confidence interval
* The baseline severity of moderate to severe vasomotor symptoms (MSVS) is the average
severity of MSVS during the two weeks between screening and randomization.
† Denotes statistical significance at the 0.050 level.
‡ p values and confidence intervals are from a two-way ANOVA with factors for treatment
and study center for the difference between treatment groups in the mean change from
baseline. Confidence intervals are adjusted for multiple comparisons within each timepoint
using Dunnett’s method.
Effects on vulvar and vaginal atrophy

In the same 13-week clinical trial, vaginal superficial cells increased by a mean of 16.0% and 18.9% for Femring 0.05 mg/day and Femring 0.10 mg/day, respectively, as compared to 1.11% for placebo at week 13. A corresponding reduction in parabasal cells was observed at week 13. Vaginal pH decreased for Femring 0.05 mg/day and Femring 0.10 mg/day by a mean of 0.73 and 0.60, respectively, compared to a mean decrease of 0.25 in the placebo group.

Women’s Health Initiative Studies

The Women’s Health Initiative (WHI) enrolled approximately 27,000 predominantly healthy postmenopausal women in two substudies to assess the risks and benefits of daily oral CE (0.625 mg)-alone or in combination with MPA (2.5 mg) compared to placebo in the prevention of certain chronic diseases. The primary endpoint was the incidence of coronary heart disease [(CHD) defined as nonfatal myocardial infarction (MI), silent MI and CHD death], with invasive breast cancer as the primary adverse outcome. A “global index” included the earliest occurrence of CHD, invasive breast cancer, stroke, pulmonary embolism (PE), endometrial cancer (only in the CE plus MPA substudy), colorectal cancer, hip fracture or death due to other cause. The study did not evaluate the effects of CE or CE plus MPA on menopausal symptoms.

WHI Estrogen-Alone Substudy

The WHI estrogen-alone substudy was stopped early because an increased risk of stroke was observed, and it was deemed that no further information would be obtained regarding the risks and benefits of estrogen-alone in predetermined primary endpoints. Results of the estrogen-alone substudy, which included 10,739 women (average age of 63 years, range 50 to 79; 75.3 percent White, 15.1 percent Black, 6.1 percent Hispanic, 3.6 percent Other), after an average follow-up of 7.1 years, are presented in Table 4.

TABLE 4. Relative and Absolute Risk Seen in the Estrogen-Alone Substudy of WHI
Event | Relative Risk CE vs Placebo (95% nCI*) | CE n = 5,310 Absolute Risk Women - | Placebo n = 5,429 per 10,000 Years
CHD events† | 0.95 (0.78 - 1.16) | 54 | 57
Non-fatal MI† | 0.91 (0.73 - 1.14) | 40 | 43
CHD death† | 1.01 (0.71 - 1.43) | 16 | 16
All Stroke† | 1.33 (1.05 - 1.68) | 45 | 33
Ischemic† | 1.55 (1.19 - 2.01) | 38 | 25
Deep vein thrombosis†,‡ | 1.47 (1.06 - 2.06) | 23 | 15
Pulmonary embolism† | 1.37 (0.90 - 2.07) | 14 | 10
Invasive breast cancer† | 0.80 (0.62 - 1.04) | 28 | 34
Colorectal cancer§ | 1.08 (0.75 - 1.55) | 17 | 16
Hip fracture† | 0.65 (0.45 - 0.94) | 12 | 19
Vertebral fractures†,‡ | 0.64 (0.44 - 0.93) | 11 | 18
Lower arm/wrist fractures†,‡ | 0.58 (0.47 - 0.72) | 35 | 59
Total fractures†,‡ | 0.71 (0.64 - 0.80) | 144 | 197
Death due to other causes§,¶ | 1.08 (0.88 - 1.32) | 53 | 50
Overall mortality†,‡ | 1.04 (0.88 - 1.22) | 79 | 75
Global Index# | 1.02 (0.92 - 1.13) | 206 | 201

* Nominal confidence intervals unadjusted for multiple looks and multiple comparisons.
† Results are based on centrally adjudicated data for an average follow-up of 7.1 years.
‡ Not included in Global index.
§ Results are based on an average follow-up of 6.8 years.
¶
All deaths, except from breast or colorectal cancer, definite/probable CHD, PE or cerebrovascular disease.#
A subset of the events was combined in a “global index”, defined as the earliest occurrence of CHD
events, invasive breast cancer, stroke, pulmonary embolism, colorectal cancer, hip fracture, or death due
to other causes.

For those outcomes included in the WHI “global index” that reached statistical significance, the absolute excess risk per 10,000 women-years in the group treated with CE-alone were 12 more strokes, while the absolute risk reduction per 10,000 women-years was 7 fewer hip fractures. The absolute excess risk of events included in the “global index” was a nonsignificant 5 events per 10,000 women-years. There was no difference between the groups in terms of all-cause mortality. (See BOXED WARNINGS, WARNINGS, and PRECAUTIONS.)

No overall difference for primary CHD events (nonfatal MI, silent MI and CHD death) and invasive breast cancer incidence in women receiving CE-alone compared with placebo was reported in final centrally adjudicated results from the estrogen-alone substudy, after an average follow-up of 7.1 years (see Table 4).

Centrally adjudicated results for stroke events from the estrogen-alone substudy, after an average follow-up of 7.1 years, reported no significant difference in distribution of stroke subtype or severity, including fatal strokes, in women receiving CE-alone compared to placebo. Estrogen-alone increased the risk of ischemic stroke, and this excess was present in all subgroups of women examined (see Table 4).

Timing of the initiation of estrogen therapy relative to the start of menopause may affect the overall risk benefit profile. The WHI estrogen-alone substudy stratified by age showed in women 50-59 years of age, a non-significant trend toward reduced risk for CHD [HR 0.63 (95 percent CI 0.36-1.09) and overall mortality [HR 0.71 (95 percent CI 0.46-1.11)].

WHI Estrogen Plus Progestin Substudy

The WHI estrogen plus progestin substudy was also stopped early. According to the predefined stopping rule, after an average follow-up of 5.6 years of treatment, the increased risk of breast cancer and cardiovascular events exceeded the specified benefits included in the “global index”. The absolute excess risk of events included in the “global index” was 19 per 10,000 women-years.

For those outcomes included in the WHI “global index” that reached statistical significance after 5.6 years of follow-up, the absolute excess risks per 10,000 women-years in the group treated with CE plus MPA were 7 more CHD events, 8 more strokes, 10 more PEs, and 8 more invasive breast cancers, while the absolute risk reductions per 10,000 women-years were 6 fewer colorectal cancers and 5 fewer hip fractures.

Results of the estrogen plus progestin substudy, which included 16,608 women (average 63 years of age, range 50 to 79; 83.9 percent White, 6.8 percent Black, 5.4 percent Hispanic, 3.9 percent Other) are presented in Table 5. These results reflect centrally adjudicated data after an average follow-up of 5.6 years.

TABLE 5. Relative and Absolute Risk Seen in the Estrogen Plus Progestin Substudy of WHI at an Average of 5.6 Years*
Event | Relative Risk CE/MPA vs Placebo (95% nCI†) | CE/MPA n = 8,506 Absolute Risk Women - | Placebo n = 8,102 per 10,000 Years
CHD events | 1.23 (0.99 - 1.53) | 41 | 34
Non-fatal MI† | 1.28 (1.00 - 1.63) | 31 | 25
CHD death | 1.10 (0.70 - 1.75) | 8 | 8
All strokes | 1.31 (1.03 - 1.68) | 33 | 25
Ischemic Stroke | 1.44 (1.09 - 1.90) | 26 | 18
Deep vein thrombosis‡ | 1.95 (1.43 - 2.67) | 26 | 13
Pulmonary embolism | 2.13 (1.45 - 3.11) | 18 | 8
Invasive breast cancer§ | 1.24 (1.01 - 1.54) | 41 | 33
Colorectal cancer | 0.61 (0.42 - 0.87) | 10 | 16
Endometrial cancer‡ | 0.81 (0.48 - 1.36) | 6 | 7
Cervical cancer‡ | 1.44 (0.47 - 4.42) | 2 | 1
Hip fracture† | 0.67 (0.47 - 0.96) | 11 | 16
Vertebral fractures‡ | 0.65 (0.46 - 0.92) | 11 | 17
Lower arm/wrist fractures‡ | 0.71 (0.59 - 0.85) | 44 | 62
Total fractures‡ | 0.76 (0.69 - 0.83) | 152 | 199
Overall Mortality‡,¶ | 1.00 (0.83 - 1.19) | 52 | 52
Global Index# | 1.13 (1.02 - 1.25) | 184 | 165

* Results are based on centrally adjudicated data.
† Nominal confidence intervals unadjusted for multiple looks and multiple comparisons.
‡ Not included in Global index.
§ Includes metastatic and non-metastatic breast cancer, with the exception of in situ breast cancer.
¶
All deaths, except from breast or colorectal cancer, definite/probable CHD, PE or cerebrovascular disease.#
A subset of the events was combined in a “global index” defined as the earliest occurrence of CHD events,
invasive breast cancer, stroke, pulmonary embolism, colorectal cancer, hip fracture, or death due to other causes.

Timing of the initiation of estrogen therapy relative to the start of menopause may affect the overall risk benefit profile. The WHI estrogen plus progestin substudy stratified by age showed in women 50-59 years of age, a non-significant trend toward reduced risk for overall mortality [HR 0.69 (95 percent CI 0.44-1.07)].

Women’s Health Initiative Memory Study

The estrogen-alone Women's Health Initiative Memory Study (WHIMS), an ancillary study of WHI, enrolled 2,947 predominantly healthy hysterectomized postmenopausal women 65 years to 79 years of age and older (45 percent, age 65 to 69 years; 36 percent, 70 to 74 years; 19 percent, 75 years of age and older) to evaluate the effects of daily CE (0.625 mg) on the incidence of probable dementia (primary outcome) compared to placebo.

After an average follow-up of 5.2 years, the relative risk of probable dementia for CE-alone versus placebo was 1.49 (95 percent CI 0.83–2.66). The absolute risk of probable dementia for CE-alone versus placebo was 37 versus 25 cases per 10,000 women-years. Probable dementia as defined in this study included Alzheimer’s disease (AD), vascular dementia (VaD) and

mixed types (having features of both AD and VaD). The most common classification of probable dementia in the treatment group and the placebo group was AD. Since the ancillary study was conducted in women 65 to 79 years of age, it is unknown whether these findings apply to younger postmenopausal women. (See BOXED WARNINGS, WARNINGS, Dementia and PRECAUTIONS, Geriatric Use.)

The WHIMS estrogen plus progestin ancillary study enrolled 4,532 predominantly healthy postmenopausal women 65 years of age and older (47 percent were age 65 to 69 years of age; 35 percent were 70 to 74 years of age; and 18 percent 75 years of age and older) to evaluate the effects of daily CE (0.625 mg) plus MPA (2.5 mg) on the incidence of probable dementia (primary outcome) compared to placebo.

After an average follow-up of 4 years, the relative risk of probable dementia for CE (0.625 mg) plus MPA (2.5 mg) versus placebo was 2.05 (95 percent CI, 1.21 to 3.48). The absolute risk of probable dementia for CE (0.625 mg) plus MPA (2.5 mg) versus placebo was 45 versus 22 per 10,000 women-years. Probable dementia as defined in this study included Alzheimer’s disease (AD), vascular dementia (VaD) and mixed types (having features of both AD and VaD). The most common classification of probable dementia in the treatment group and placebo group was AD. Since the ancillary study was conducted in women 65 to 79 years of age, it is unknown whether these findings apply to younger postmenopausal women. (See BOXED WARNINGS, WARNINGS, Dementia and PRECAUTIONS, Geriatric Use.)

When data from the two populations were pooled as planned in the WHIMS protocol, the reported overall relative risk for probable dementia was 1.76 (95 percent CI 1.19-2.60). Differences between groups became apparent in the first year of treatment. It is unknown whether these findings apply to younger postmenopausal women. (See BOXED WARNINGS, WARNINGS, Dementia and PRECAUTIONS, Geriatric Use.)

INDICATIONS AND USAGE

Femring therapy is indicated in the:

1. Treatment of moderate to severe vasomotor symptoms due to menopause.

2. Treatment of moderate to severe vulvar and vaginal atrophy due to menopause.

CONTRAINDICATIONS

Femring should not be used in women with any of the following conditions:

1. Undiagnosed abnormal genital bleeding.
2. Known, suspected, or history of breast cancer.
3. Known or suspected estrogen-dependent neoplasia.
4. Active deep vein thrombosis, pulmonary embolism or history of these conditions.
5. Active arterial thromboembolic disease (for example, stroke and myocardial infarction) or a history of these conditions.
6. Known liver dysfunction or disease.
7. Known or suspected pregnancy.

WARNINGS

SeeBOXED WARNINGS

Femring is used only in the vagina, however, the risks associated with oral estrogens should be taken into account.

1. Cardiovascular disorders

An increased risk of stroke and deep vein thrombosis (DVT) has been reported with estrogen-alone therapy. An increased risk of pulmonary embolism, DVT, stroke, and myocardial infarction has been reported with estrogen plus progestin therapy. Should any of these events occur or be suspected, estrogens with or without progestins should be discontinued immediately.

Risk factors for arterial vascular disease (for example, hypertension, diabetes mellitus, tobacco use, hypercholesterolemia and obesity) and/or venous thromboembolism (for example, personal history or family history of VTE, obesity and systemic lupus erythematosus) should be managed appropriately.

a. Stroke

In the Women's Health Initiative (WHI) estrogen-alone substudy, a statistically significant increased risk of stroke was reported in women 50 to 79 years of age receiving daily conjugated estrogens CE (0.625 mg) compared to women of the same age receiving placebo (45 versus 33 per 10,000 women-years). The increase in risk was demonstrated in year one and persisted. (See CLINICAL STUDIES.) Should a stroke occur or be suspected, estrogens should be discontinued immediately.

Sub-group analyses of women 50 to 59 years of age suggest no increased risk of stroke for those women receiving CE (0.625 mg) versus those receiving placebo (18 versus 21 per 10,000 women-years).

In the WHI estrogen plus progestin substudy, a statistically significant increased risk of stroke was reported in all women receiving daily CE (0.625 mg) plus MPA (2.5 mg) compared to placebo (33 versus 25 per 10,000 women-years). The increase in risk was demonstrated after the first year and persisted. (See CLINICAL STUDIES.)

b. Coronary heart disease

In the WHI estrogen-alone substudy, no overall effect on coronary heart disease (CHD) events (defined as nonfatal myocardial infarction [MI], silent MI, or CHD death) was reported in women receiving estrogen-alone compared to placebo. (See CLINICAL STUDIES.)

Subgroup analyses of women 50 to 59 years of age suggest a statistically non-significant reduction in CHD events (CE 0.625 mg compared to placebo) in women with less than 10 years since menopause (8 versus 16 per 10,000 women-years).

In the WHI estrogen plus progestin substudy, there was a statistically non-significant increased risk of CHD events in women receiving daily CE (0.625 mg) plus MPA (2.5 mg) compared to women receiving placebo (41 versus 34 per 10,000 women-years). An increase in relative risk was demonstrated in year 1, and a trend toward decreasing relative risk was reported in years 2 through 5.

In postmenopausal women with documented heart disease (n = 2,763, average age 66.7 years), in a controlled clinical trial of secondary prevention of cardiovascular disease (Heart and Estrogen/Progestin Replacement Study; HERS), treatment with daily CE (0.625 mg) plus MPA (2.5 mg) demonstrated no cardiovascular benefit. During an average follow-up of 4.1 years, treatment with CE plus MPA did not reduce the overall rate of CHD events in postmenopausal women with established coronary heart disease. There were more CHD events in the CE plus MPA-treated group than in the placebo group in year 1, but not during the subsequent years. Two thousand three hundred and twenty one (2,321) women from the original HERS trial agreed to participate in an open-label extension of HERS, HERS II. Average follow-up in HERS II was an additional 2.7 years, for a total of 6.8 years overall. Rates of CHD events were comparable among women in the CE/MPA group and the placebo group in the HERS, the HERS II, and overall.

c. Venous thromboembolism (VTE)

In the WHI estrogen-alone substudy, the risk of VTE (DVT and pulmonary embolism [PE]), was increased for women receiving daily CE (0.625 mg) compared to placebo (30 versus 22 per 10,000 women-years), although only the increased risk of DVT reached statistical significance (23 versus 15 per 10,000 women-years). The increase in VTE risk was demonstrated during the first 2 years. (See CLINICAL STUDIES.) Should a VTE occur or be suspected, estrogens should be discontinued immediately.

In the WHI estrogen plus progestin substudy, a statistically significant 2-fold greater rate of VTE was reported in women receiving daily CE (0.625 mg) plus MPA (2.5 mg) compared to women receiving placebo (35 versus 17 per 10,000 women-years). Statistically significant increases in risk for both DVT (26 versus 13 per 10,000 women-years) and PE (18 versus 8 per 10,000 women-years) were also demonstrated. The increase in VTE risk was observed during the first year and persisted. (See CLINICAL STUDIES.) Should a VTE occur or be suspected, estrogens should be discontinued immediately.

If feasible, estrogens should be discontinued at least 4 to 6 weeks before surgery of the type associated with an increased risk of thromboembolism or during periods of prolonged immobilization.

2. Malignant neoplasmsa. Endometrial cancer

An increased risk of endometrial cancer has been reported with the use of unopposed estrogen therapy in a woman with a uterus. The reported endometrial cancer risk among unopposed estrogen users is about 2- to 12-fold greater than in nonusers, and appears dependent on duration of treatment and on estrogen dose. Most studies show no significant increased risk associated with use of estrogens for less than one year. The greatest risk appears associated with prolonged use, with increased risks of 15- to 24-fold for five to ten years or more, and this risk has been shown to persist for at least 8 to 15 years after estrogen therapy is discontinued.

Clinical surveillance of all women using estrogen-alone or estrogen plus progestin therapy is important. Adequate diagnostic measures, including directed or random endometrial sampling when indicated, should be undertaken to rule out malignancy in all cases of undiagnosed persistent or recurring abnormal genital bleeding.

There is no evidence that the use of natural estrogens results in a different endometrial risk profile than synthetic estrogens of equivalent estrogen dose. Adding a progestin to estrogen therapy has been shown to reduce the risk of endometrial hyperplasia, which may be a precursor to endometrial cancer.

b. Breast cancer

The most important randomized clinical trial providing information about breast cancer in estrogen-alone users is the Women’s Health Initiative (WHI) substudy of daily CE (0.625 mg). In the WHI estrogen-alone substudy, after an average of 7.1 years of follow-up, daily CE (0.625 mg) was not associated with an increased risk of invasive breast cancer (relative risk [RR] 0.80). (See CLINICAL STUDIES.)

The most important clinical trial providing information about breast cancer in estrogen plus progestin users is the WHI substudy of daily CE (0.625 mg) plus MPA (2.5 mg). After a mean follow-up of 5.6 years, the estrogen plus progestin substudy reported an increased risk of breast cancer in women who took daily CE plus MPA. In this substudy, prior use of estrogen-alone or estrogen plus progestin therapy was reported by 26 percent of the women. The relative risk of invasive breast cancer was 1.24, and the absolute risk was 41 versus 33 cases per 10,000 women-years for estrogen plus progestin compared with placebo. Among women who reported prior use of hormone therapy, the relative risk of invasive breast cancer was 1.86 and the absolute risk was 46 versus 25 cases per 10,000 women-years for estrogen plus progestin compared with placebo. Among women who reported no prior use of hormone therapy, the relative risk of invasive breast cancer was 1.09, and the absolute risk was 40 versus 36 cases per 10,000 women-years for estrogen plus progestin compared with placebo. In the same substudy, invasive breast cancers were larger and diagnosed at a more advanced stage in the CE (0.625 mg) plus MPA (2.5 mg) group compared with the placebo group. Metastatic disease was rare with no apparent difference between the two groups. Other prognostic factors, such as histologic subtype, grade and hormone receptor status did not differ between the groups. (See CLINICAL STUDIES.)

Consistent with the WHI clinical trial, observational studies have also reported an increased risk of breast cancer for estrogen plus progestin therapy, and a smaller increased risk for estrogen-alone therapy, after several years of use. The risk increased with duration of use, and appeared to return to baseline over about 5 years after stopping treatment (only the observational studies have substantial data on risk after stopping). Observational studies also suggest that the risk of breast cancer was greater, and became apparent earlier, with estrogen plus progestin therapy as compared to estrogen-alone therapy. However, these studies have not generally found significant variation in the risk of breast cancer among different estrogens or among different estrogen plus progestin combinations, doses, or routes of administration.

The use of estrogen-alone and estrogen plus progestin has been reported to result in an increase in abnormal mammograms requiring further evaluation.

All women should receive yearly breast examinations by a healthcare provider and perform monthly breast self-examinations. In addition, mammography examinations should be scheduled based on patient age, risk factors and prior mammogram results.

c. Ovarian cancer

The WHI estrogen plus progestin substudy reported a statistically non-significant increased risk of ovarian cancer. After an average follow-up of 5.6 years, the relative risk for ovarian cancer for CE plus MPA versus placebo was 1.58 (95 percent nCI 0.77-3.24). The absolute risk for CE plus MPA versus placebo was 4 versus 3 cases per 10,000 women-years. In some epidemiologic studies, the use of estrogen-only products, in particular for 5 or more years, has been associated with an increased risk of ovarian cancer. However, the duration of exposure associated with increased risk is not consistent across all epidemiologic studies and some report no association.

3. Probable Dementia

In the estrogen-alone Women's Health Initiative Memory Study (WHIMS), an ancillary study of WHI, a population of 2,947 hysterectomized women 65 to 79 years of age was randomized to daily CE (0.625 mg) or placebo. In the WHIMS estrogen plus progestin ancillary study, a population of 4,532 postmenopausal women 65 to 79 years of age was randomized to daily CE (0.625 mg) plus MPA (2.5 mg) or placebo.

In the WHIMS estrogen-alone ancillary study, after an average follow-up of 5.2 years, 28 women in the estrogen-alone group and 19 women in the placebo group were diagnosed with probable dementia. The relative risk of probable dementia for CE-alone versus placebo was 1.49 (95 percent nCI 0.83-2.66). The absolute risk of probable dementia for CE-alone versus placebo was 37 versus 25 cases per 10,000 women-years. (See CLINICAL STUDIES and PRECAUTIONS, Geriatric Use.)

In the WHIMS estrogen plus progestin ancillary study, after an average follow-up of 4 years, 40 women in the CE plus MPA group and 21 women in the placebo group were diagnosed with probable dementia. The relative risk of probable dementia for CE plus MPA versus placebo was 2.05 (95 percent nCI 1.21-3.48). The absolute risk of probable dementia for CE plus MPA versus placebo was 45 versus 22 cases per 10,000 women-years. (See CLINICAL STUDIES and PRECAUTIONS, Geriatric Use.)

When data from the two populations were pooled as planned in the WHIMS protocol, the reported overall relative risk for probable dementia was 1.76 (95 percent nCI 1.19-2.60). Since both substudies were conducted in women aged 65 to 79 years, it is unknown whether these findings apply to younger postmenopausal women. (See BOXED WARNINGS and PRECAUTIONS, Geriatric Use.)

4. Gallbladder disease

A 2- to 4-fold increase in the risk of gallbladder disease requiring surgery in postmenopausal women receiving estrogens has been reported.

5. Hypercalcemia

Estrogen administration may lead to severe hypercalcemia in women with breast cancer and bone metastases. If hypercalcemia occurs, use of the drug should be stopped and appropriate measures taken to reduce the serum calcium level.

6. Visual abnormalities

Retinal vascular thrombosis has been reported in women receiving estrogens. Discontinue medication pending examination if there is sudden partial or complete loss of vision, or a sudden onset of proptosis, diplopia or migraine. If examination reveals papilledema or retinal vascular lesions, estrogens should be permanently discontinued.

PRECAUTIONS

A. General

1. Addition of a progestin when a woman has not had a hysterectomy

Studies of the addition of a progestin for 10 or more days of a cycle of estrogen administration, or daily with estrogen in a continuous regimen, have reported a lowered incidence of endometrial hyperplasia than would be induced by estrogen treatment alone. Endometrial hyperplasia may be a precursor to endometrial cancer.

There are, however, possible risks that may be associated with the use of progestins with estrogens compared to estrogen-alone regimens. These include an increased risk of breast cancer.

2. Elevated blood pressure

In a small number of case reports, substantial increases in blood pressure have been attributed to idiosyncratic reactions to estrogens. In a large, randomized, placebo-controlled clinical trial, a generalized effect of estrogens on blood pressure was not seen.

3. Hypertriglyceridemia

In patients with pre-existing hypertriglyceridemia, estrogen therapy may be associated with elevations of plasma triglycerides leading to pancreatitis. Consider discontinuation of treatment if pancreatitis develops.

4. Hepatic impairment and/or a past history of cholestatic jaundice

Estrogens may be poorly metabolized in women with impaired liver function. For women with a history of cholestatic jaundice associated with past estrogen use or with pregnancy, caution should be exercised and in the case of recurrence, medication should be discontinued.

5. Hypothyroidism

Estrogen administration leads to increased thyroid-binding globulin (TBG) levels. Women with normal thyroid function can compensate for the increased TBG by making more thyroid hormone, thus maintaining free T4 and T3 serum concentrations in the normal range. Women dependent on thyroid hormone replacement therapy who are also receiving estrogens may require increased doses of their thyroid replacement therapy. These women should have their thyroid function monitored in order to maintain their free thyroid hormone levels in an acceptable range.

6. Fluid retention

Estrogens may cause some degree of fluid retention. Women with conditions that might be influenced by this factor, such as cardiac or renal dysfunction, warrant careful observation when estrogens are prescribed.

7. Hypocalcemia

Estrogens should be used with caution in women with hypoparathyroidism as estrogen-induced hypocalcemia may occur.

8. Exacerbation of endometriosis

A few cases of malignant transformation of residual endometrial implants have been reported in women treated post-hysterectomy with estrogen-alone therapy. For women known to have residual endometriosis post-hysterectomy, the addition of progestin should be considered.

9. Exacerbation of other conditions

Estrogen therapy may cause an exacerbation of asthma, diabetes mellitus, epilepsy, migraine, porphyria, systemic lupus erythematosus and hepatic hemangiomas, and should be used with caution in women with these conditions.

10. Vaginal use and expulsion

Femring may not be suitable for women with conditions that make the vagina more susceptible to vaginal irritation or ulceration, or make expulsions more likely, such as narrow vagina, vaginal stenosis, vaginal infection, cervical prolapse, rectoceles and cystoceles. If local treatment of a vaginal infection is required, Femring can remain in place during treatment.

B. Patient Information

Physicians are advised to discuss the PATIENT INFORMATION leaflet with patients for whom they prescribe Femring.

C. Laboratory Tests

Serum follicle stimulating hormone and estradiol levels have not been shown to be useful in the management of moderate to severe symptoms of vulvar and vaginal atrophy.

D. Drug/Laboratory Test Interactions

1. Accelerated prothrombin time, partial thromboplastin time, and platelet aggregation time; increased platelet count; increased factors II, VII antigen, VIII antigen, VIII coagulant activity, IX, X, XII, VII-X complex, II-VII-X complex, and beta-thromboglobulin; decreased levels of antifactor Xa and antithrombin III, decreased antithrombin III activity; increased levels of fibrinogen and fibrinogen activity; increased plasminogen antigen and activity.
2. Increased thyroid-binding globulin (TBG) levels leading to increased circulating total thyroid hormone levels as measured by protein-bound iodine (PBI), T4 levels (by column or by radioimmunoassay) or T3 levels by radioimmunoassay. T3 resin uptake is decreased, reflecting the elevated TBG. Free T4 and free T3 concentrations are unaltered. Women on thyroid replacement therapy may require higher doses of thyroid hormone.
3. Other binding proteins may be elevated in serum, for example, corticosteroid binding globulin (CBG), sex hormone binding globulin (SHBG)) leading to increased total circulating corticosteroids and sex steroids, respectively. Free hormone concentrations, such as testosterone and estradiol, may be decreased. Other plasma proteins may be increased (angiotensinogen/renin substrate, alpha-1-antitrypsin, ceruloplasmin).
4. Increased plasma HDL and HDL2 cholesterol subfraction concentrations, reduced LDL cholesterol concentration, increased triglycerides levels.
5. Impaired glucose tolerance.

E. Carcinogenesis, Mutagenesis, Impairment of Fertility

Long-term continuous administration of natural and synthetic estrogens in certain animal species increases the frequency of carcinomas of the breast, uterus, cervix, vagina, testis, and liver.

Estradiol acetate was assayed for mutation in four histidine-requiring strains of Salmonella typhimurium and in two tryptophan-requiring strains of Escherichia coli. Estradiol acetate did not induce mutation in any of the bacterial strains tested under the conditions employed.

F. Pregnancy

Femring should not be used during pregnancy. (See CONTRAINDICATIONS.)

There appears to be little or no increased risk of birth defects in children born to women who have used estrogens and progestins as an oral contraceptive inadvertently during early pregnancy.

G. Nursing Mothers

Femring should not be used during lactation. Estrogen administration to nursing mothers has been shown to decrease the quantity and quality of the breast milk. Detectable amounts of estrogens have been identified in the milk of mothers receiving estrogens.

H. Pediatric Use

Femring is not indicated in children. Clinical studies have not been conducted in the pediatric population.

I. Geriatric Use

There have not been sufficient numbers of geriatric women involved in clinical studies utilizing Femring to determine whether those over 65 years of age differ from younger subjects in their response to Femring.

The Women’s Health Initiative Study

In the Women's Health Initiative (WHI) estrogen-alone substudy (daily conjugated estrogens 0.625 mg versus placebo), there was a higher relative risk of stroke in women greater than 65 years of age.

In the WHI estrogen plus progestin substudy, there was a higher relative risk of nonfatal stroke and invasive breast cancer in women greater than 65 years of age.

The Women’s Health Initiative Memory Study

In the Women’s Health Initiative Memory Study (WHIMS) of postmenopausal women 65 to 79 years of age, there was an increased risk of developing probable dementia in the estrogen-alone and the estrogen plus progestin groups when compared to placebo.

Since both substudies were conducted in women 65 to 79 years of age, it is unknown whether these findings apply to younger postmenopausal women.

ADVERSE REACTIONS

See BOXED WARNINGS, WARNINGSand PRECAUTIONS.

Because clinical trials are conducted under widely varying conditions, adverse reaction rates observed in the clinical trials of a drug cannot be directly compared to rates in the clinical trials of another drug and may not reflect the rates observed in practice.

In a 13-week clinical trial that included 225 postmenopausal women treated with Femring and 108 women treated with placebo vaginal rings, adverse events that occurred at a rate of ≥ 2 percent are summarized in Table 6.

Table 6. Incidence of AEs Occurring in ≥ 2% of Subjects Presented in Descending Frequency of Preferred Term
Adverse Event | Placebo (n = 108) | Estradiol 0.05 mg/day (n = 113) | Estradiol 0.10 mg/day (n = 112)
 | n (%) | n (%) | n (%)
Headache (NOS) | 10 (9.3) | 8 (7.1) | 11 (9.8)
Intermenstrual Bleeding | 2 (1.9) | 9 (8.0) | 11 (9.8)
Vaginal Candidiasis | 3 (2.8) | 7 (6.2) | 12 (10.7)
Breast Tenderness | 2 (1.9) | 7 (6.2) | 12 (10.7)
Back Pain | 4 (3.7) | 7 (6.2) | 4 (3.6)
Genital Disorder Femal (NOS) | 9 (8.3) | 3 (2.7) | 3 (2.7)
Upper Respiratory Tract Infection (NOS) | 6 (5.6) | 5 (4.4) | 4 (3.6)
Abdominal Distension | 3 (2.8) | 8 (7.1) | 3 (2.7)
Vaginal discharge | 9 (8.3) | 2 (1.8) | 3 (2.7)
Vulvovaginitis (NOS) | 7 (6.5) | 6 (5.3) | 1 (0.9)
Nausea | 5 (4.6) | 3 (2.7) | 2 (1.8)
Arthralgia | 4 (3.7) | 2 (1.8) | 2 (1.8)
Sinusitis (NOS) | 2 (1.9) | 2 (1.8) | 4 (3.6)
Uterine Pain | 1 (0.9) | 2 (1.8) | 5 (4.5)
Nasopharyngitis | 3 (2.8) | 2 (1.8) | 2 (1.8)
Pain in Limb | 3 (2.8) | 1 (0.9) | 3 (2.7)
Urinary Tract Infection (NOS) | 2 (1.9) | 1 (0.9) | 4 (3.6)
Vaginal Irritation | 4 (3.7) | 1 (0.9) | 2 (1.8)

Postmarketing Experience

1. A few cases of toxic shock syndrome (TSS) have been reported in women using vaginal rings. TSS is a rare, but serious disease that may cause death. Warning signs of TSS include fever, nausea, vomiting, diarrhea, muscle pain, dizziness, faintness, or a sunburn-rash on face and body.
2. A few cases of ring adherence to the vaginal or bladder wall, making ring removal difficult, have been reported in women using vaginal rings. Patients should be carefully evaluated for vaginal or bladder wall ulceration or erosion. If an ulceration or erosion has occurred, consideration should be given to leaving the ring out and not replacing it until healing is complete to prevent the ring from adhering to the vaginal tissue.
3. A few cases of bowel obstruction associated with vaginal ring use have been reported. Persistent abdominal complaints consistent with obstruction should be carefully evaluated.
4. A few cases of inadvertent ring insertion into the urinary bladder, which may require surgical removal, have been reported for women using vaginal rings. Persistent unexplained urinary symptoms should be carefully evaluated.

The following additional adverse reactions have been identified during post-approval use of Femring. Because these reactions are reported voluntarily from a population of uncertain size, it is not always possible to reliably estimate their frequency or establish a causal relationship to drug exposure.

1. Genitourinary system

Uterine cancer, vaginal hemorrhage, ovarian cyst, irregular menstruation, metrorrhagia, menorrhagia, dysmenorrhea, uterine enlargement.

2. Breasts

Breast cancer, fibrocystic breast disease, breast disorder, breast mass, breast enlargement, breast pain, nipple pain, breast discharge.

3. Cardiovascular

Chest pain, increased blood pressure, irregular heart rate, pulmonary embolism, cerebrovascular accident (stroke), hemiparesis, transient ischemic attack, thrombosis.

4. Gastrointestinal

Abdominal pain, pancreatitis, cholecystitis, cholelithiasis, vomiting.

5. Skin

Generalized erythema, erythema multiforme, erythema nodosum, rash, hirsutism, pruritis.

6. Eyes

Blindness, contact lens intolerance.

7. Central Nervous System

Dizziness, headache, depression, nervousness, mood disturbances, irritability.

8. Miscellaneous

Medical device complication, back pain, angioedema, weight increased/decreased, edema, libido increased/decreased, urticaria, hypersensitivity, anaphylaxis.

OVERDOSAGE

Overdosage of estrogen may cause nausea and vomiting, breast tenderness, dizziness, abdominal pain, drowsiness/fatigue and withdrawal bleeding may occur in women. Treatment of overdose consists of discontinuation of Femring with institution of appropriate symptomatic care.

DOSAGE AND ADMINISTRATION

Generally, when estrogen is prescribed for a postmenopausal woman with a uterus, a progestin should also be considered to reduce the risk of endometrial cancer. A woman without a uterus does not need a progestin. In some cases, however, hysterectomized women with a history of endometriosis may need a progestin.

Use of estrogen-alone, or in combination with a progestin, should be with the lowest effective dose and for the shortest duration consistent with treatment goals and risks for the individual woman. Postmenopausal women should be re-evaluated periodically as clinically appropriate to determine if treatment is still necessary. (See BOXED WARNINGS and WARNINGS.)

Two doses of Femring are available, 0.05 mg/day and 0.10 mg/day, for the treatment of moderate to severe vasomotor symptoms and/or vulvar and vaginal atrophy due to menopause.

Patients should be started at the lowest dose. The lowest effective dose of Femring has not been determined.

Instructions for Use

Hands should be thoroughly washed before and after ring insertion.

Femring Insertion

Insert upon removal from the protective pouch.

The opposite sides of the vaginal ring should be pressed together and inserted into the vagina. The exact position is not critical to its function. When Femring is in place, the patient should not feel anything. If the patient feels discomfort, the vaginal ring is probably not far enough inside the vagina. Gently push Femring further into the vagina.

Femring Use

Femring should remain in place for 3 months and then be replaced by a new Femring.

The patient should not feel Femring when it is in place and it should not interfere with sexual intercourse. Straining upon bowel movement may make Femring move down in the lower part of the vagina. If so, it may be repositioned with a finger.

If Femring is expelled totally from the vagina, it should be rinsed in lukewarm water and reinserted by the patient (or healthcare provider if necessary).

Femring Removal

Femring may be removed by looping a finger through the ring and pulling it out.

For patient instructions, see PATIENT INFORMATION.

HOW SUPPLIED

Each Femring® (estradiol acetate vaginal ring) is individually packaged in a pouch consisting of one side medical grade paper and the other side polyester/polyethylene laminate.

NDC 54868-6030-0 Femring® 0.10 mg/day (estradiol acetate vaginal ring) is available in single units.

Relabeling of "Additional Barcode" by
Physicians Total Care, Inc.
Tulsa, OK 74146

STORAGE

Store at 25˚ C (77˚ F); excursions permitted to 15˚ - 30˚ C (59˚ - 86˚ F) [see USP Controlled Room Temperature].

PATIENT INFORMATION

Femring® (estradiol acetate vaginal ring)

Read this PATIENT INFORMATION before you start using Femring and read what you get each time you refill your Femring prescription. There may be new information. This information does not take the place of talking to your healthcare provider about your medical condition or your treatment.

What is the most important information I should know about Femring (an estrogen product)?

- Using estrogen-alone therapy increases your chance of getting cancer of the uterus (womb).

Report any unusual vaginal bleeding right away while you are using Femring. Vaginal bleeding after menopause may be a warning sign of cancer of the uterus (womb). Your healthcare provider should check any unusual vaginal bleeding to find out the cause.

- Do not use estrogen-alone therapy to prevent heart disease, heart attacks or dementia (decline of brain function).
- Using estrogen-alone therapy may increase your chances of getting strokes or blood clots.
- Using estrogen-alone therapy may increase your chance of getting dementia, based on a study of women age 65 or older.
- Do not use estrogens with progestins to prevent heart disease, heart attacks, or dementia.
- Using estrogens with progestins may increase your chances of getting heart attacks, strokes, breast cancer, or blood clots.
- Using estrogens with progestins may increase your chance of getting dementia, based on a study of women age 65 years or older.
- You and your healthcare provider should talk regularly about whether you still need treatment with Femring.

What is Femring?

Femring (estradiol acetate vaginal ring) is an off-white, soft, flexible vaginal ring with a center that contains an estrogen. Femring should be removed after 90 days of continuous use. If continuation of therapy is indicated, a new flexible ring should be replaced.

What is Femring used for?

Femring is used after menopause to:

- reduce moderate to severe hot flashes

Estrogens are hormones made by a woman’s ovaries. The ovaries normally stop making estrogens when a woman is between 45 to 55 years old. This drop in body estrogen levels causes the "change of life" or menopause (the end of monthly menstrual periods). Sometimes, both ovaries are removed during an operation before natural menopause takes place. The sudden drop in estrogen levels causes "surgical menopause".

When the estrogen levels begin dropping, some women develop very uncomfortable symptoms, such as feelings of warmth in the face, neck, and chest, or sudden strong feelings of heat and sweating ("hot flashes" or "hot flushes"). In some women the symptoms are mild and they will not need estrogens. In other women, symptoms can be more severe. You and your healthcare provider should talk regularly about whether you still need treatment with Femring.

- treat menopausal changes in and around the vagina

You and your healthcare provider should talk regularly about whether you still need treatment with Femring to control these problems.

Who should not use Femring?

Do not start using Femring if you:

- Have unusual vaginal bleeding
- Currently have or have had certain cancers
  Estrogens may increase the chances of getting certain types of cancers including cancer of the breast or uterus. If you have or had cancer, talk with your healthcare provider about whether you should use Femring.
- Had a stroke or heart attack
- Currently have or have had blood clots
- Currently have or have had liver problems
- Are allergic to any of the ingredients in Femring. See the list of ingredients in Femring at the end of this leaflet.
- Think you may be pregnant

Tell your healthcare provider:

- If you have any unusual vaginal bleeding. Vaginal bleeding after menopause may be a warning sign of cancer of the uterus (womb). Your healthcare provider should check any unusual vaginal bleeding to find out the cause.
- About all of your medical problems. Your healthcare provider may need to check you more carefully if you have certain conditions, such as asthma (wheezing), epilepsy (seizures), diabetes, migraine, endometriosis, lupus, or problems with your heart, liver, thyroid, kidneys or have high calcium levels in your blood.
- About all the medicines you take. This includes prescription and nonprescription medicines, vitamins and herbal supplements. Some medicines may affect how Femring works. Femring may also affect how your other medicines work.
- If you are going to have surgery or will be on bed rest. You may need to stop taking estrogens.
- If you are breastfeeding. The hormone in Femring can pass into your milk.

How should I use Femring?

1. Start at the lowest dose and talk to your healthcare provider about how well that dose is working for you.
2. Estrogens should be used at the lowest dose possible for your treatment only as long as needed. The lowest effective dose of Femring has not been determined. You and your healthcare provider should talk regularly (for example, every 3 to 6 months) about the dose you are using and whether you still need treatment with Femring.

- Femring is inserted into your vagina by you or your healthcare provider.
- Femring should stay in your vagina for 3 months.
- After 3 months Femring should be removed and a new Femring should be inserted.

To insert Femring into your vagina:

1. Wash and dry your hands.
2. Remove Femring from its pouch.
3. Choose the position that is most comfortable for you. For example, lying down or standing with one leg up (Diagrams 1a and 1b, respectively).

DIAGRAM 1a

DIAGRAM 1b

4. Use your thumb and index finger (pointer finger) to press the sides of the ring together. You may find it easier to insert Femring if you twist it into a figure-of-eight shape (Diagram 2).

DIAGRAM 2

5. Use your other hand and hold open the folds of skin around your vagina (Diagram 3).

DIAGRAM 3

6. Place the tip of the ring in the vaginal opening and then use your index finger to push the folded ring gently into your vagina. Push it up towards your lower back as far as you can (Diagram 4).

DIAGRAM 4

If the ring feels uncomfortable, you probably did not push it into your vagina far enough. Use your index finger to push the ring as far as you can into your vagina (Diagram 5). There is no danger of Femring being pushed too far up in the vagina or getting lost.

DIAGRAM 5

Femring should now be in your upper vagina (Diagram 6). The exact position of Femring in the vagina is not important for it to work.

DIAGRAM 6

7. Wash your hands when you are done.

After 3 months, Femring may no longer release enough medicine to control your menopausal symptoms. To continue to have symptom relief your current Femring should be removed and replaced with a new one if you and your healthcare provider have decided that you still need treatment with Femring.

To remove Femring:

1. Wash and dry your hands.

2. Choose the position that is most comfortable for you (see Diagrams 1a and 1b).

3. Put a finger into your vagina and hook it through the ring. (Diagram 7).

DIAGRAM 7

4. Gently pull downwards and forwards to remove Femring.

5. Wrap the used ring in tissue or toilet paper and put it in a trash can.

6. Wash your hands.

Insert another ring now if your healthcare provider has told you to.

If your Femring comes out of your vagina before 3 months, clean it with warm water and put it back in your vagina.

- Femring can come out if it is not put in far enough.
- Femring can come out when you are pushing hard during a bowel movement.
- Femring can come out if your vaginal muscles are weak.

If Femring comes out often, tell your healthcare provider. Femring may not be right for you.

Call your healthcare provider if you have any problems putting Femring in your vagina or taking it out.

You may leave Femring in place if you need to use medicine for a vaginal infection.

You may leave Femring in place during sex (intercourse). If you take Femring out during intercourse or it comes out, clean it with warm water and put it back in your vagina.

If you lose your Femring, a new Femring should be put in place for 3 months.

What are the possible side effects of vaginal rings?

A few cases of toxic shock syndrome (TSS) have been reported in women using vaginal rings. Toxic shock syndrome is a rare but serious illness caused by a bacterial infection. If you have fever, nausea, vomiting, diarrhea, muscle pain, dizziness, faintness, or a sunburn-rash on face and body, remove Femring and contact your healthcare provider. A few cases of a vaginal ring becoming attached to the vaginal wall, making ring removal difficult, have been reported. Rare cases of a vaginal ring being inserted into the bladder, instead of the vagina, also have been reported.

What are the possible side effects of estrogens?

Side effects are grouped by how serious they are and how often they happen when you are treated.

Serious but less common side effects include:

- Breast cancer
- Cancer of the uterus
- Stroke
- Heart attack
- Blood clots
- Dementia
- Gallbladder disease
- Ovarian cancer
- High blood pressure
- Liver problems
- High blood sugar
- Enlargement of benign tumors of the uterus (“fibroids”)

Some of the warning signs of serious side effects include:

- Breast lumps
- Unusual vaginal bleeding
- Dizziness and faintness
- Changes in speech
- Severe headaches
- Chest pain
- Shortness of breath
- Pains in your legs
- Changes in vision
- Vomiting
- Yellowing of the skin, eyes or nail beds

Call your healthcare provider right away if you get any of these warning signs or any other unusual symptom that concerns you.

Less serious but common side effects include:

- Headache
- Breast pain
- Irregular vaginal bleeding or spotting
- Stomach/abdominal cramps, bloating
- Nausea and vomiting
- Hair loss
- Fluid retention
- Vaginal yeast infection
- Reactions from inserting Femring such as burning, irritation, and itching

These are not all the possible side effects of Femring. For more information, ask your healthcare provider or pharmacist.

What can I do to lower my chances of getting a serious side effect with Femring?

- Talk with your healthcare provider regularly about whether you should continue using Femring.
- If you have a uterus, talk to your healthcare provider about whether the addition of a progestin is right for you. The addition of a progestin is generally recommended for a woman with a uterus to reduce the chance of getting cancer of the uterus. See your healthcare provider right away if you get vaginal bleeding while using Femring.
- If you have fever, nausea, vomiting, diarrhea, muscle pain, dizziness, faintness, or a sunburn-rash on face and body, remove Femring and contact your healthcare provider.
- Contact your healthcare provider right away if you have difficulty removing Femring.
- Have a pelvic exam, breast exam and mammogram (breast x-ray) every year unless your healthcare provider tells you something else. If members of your family have had breast cancer or if you have ever had breast lumps or an abnormal mammogram, you may need to have breast examinations more often.
- If you have high blood pressure, high cholesterol (fat in the blood), diabetes, are overweight, or if you use tobacco, you may have higher chances of getting heart disease. Ask your healthcare provider for ways to lower your chances for getting heart disease.

General information about safe and effective use of Femring.

Medicines are sometimes prescribed for conditions that are not mentioned in patient information leaflets. Do not use Femring for conditions for which it was not prescribed. Do not give Femring to other people, even if they have the same symptoms you have. It may harm them.

Keep Femring out of the reach of children.

This leaflet provides a summary of the most important information about Femring. If you would like more information, talk with your healthcare provider or pharmacist. You can ask for information about Femring that is written for health professionals. You can get more information by calling the toll free number 800-521-8813.

What are the ingredients in Femring?

Femring contains estradiol acetate, an estrogen. It also contains cured silicone elastomer composed of dimethyl polysiloxane silanol, silica (diatomaceous earth), normal propyl orthosilicate, stannous octoate; and barium sulfate. There are no coloring agents in Femring.

Manufactured by: Warner Chilcott UK, Ltd., Larne, Northern Ireland, UK

Marketed by: Warner Chilcott (US), LLC, Rockaway, NJ 07866

1-800-521-8813

To report SUSPECTED ADVERSE REACTIONS, contact Warner Chilcott at 1-800-521-8813 or FDA at 1-800-FDA-1088 or www.fda.gov/medwatch.

6201G071

REVISED September 2009

PRINCIPAL DISPLAY PANEL

Femring

(estradiol acetate vaginal ring)

0.10 mg/day

Rx ONLY

(Contains 24.8 mg estradiol acetate to deliver the equivalent of 0.10 mg estradiol per day for three months.)

Other ingredients: barium sulfate and cured elastomer.

Store at 25oC (77oF); excursions permitted to 15o - 30oC (59o - 86oF).

[see USP Controlled Room Temperature]

For intravaginal use only.

CONTENTS: 1 VAGINAL RING